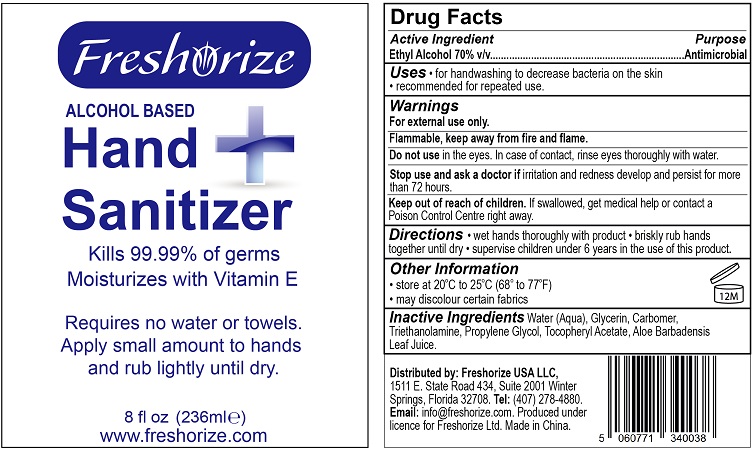 DRUG LABEL: Freshorize Hand Sanitizer Moisturizing with Vitamin E
NDC: 74149-001 | Form: GEL
Manufacturer: Yiwu Yangjie Daily Chemicals Co.,Ltd.
Category: otc | Type: HUMAN OTC DRUG LABEL
Date: 20200410

ACTIVE INGREDIENTS: alcohol 70 mL/100 mL
INACTIVE INGREDIENTS: WATER; PROPYLENE GLYCOL; ALOE VERA LEAF; CARBOMER 934; GLYCERIN; .ALPHA.-TOCOPHEROL ACETATE

Drug facts

Active ingredient Purpose

Ethyl Alcohol 70% ... Antimicrobial

PURPOSE

- for Handwashing to help decrease bacteria on the skin.
- recommended for repeated use.

KEEP OUT OF REACH OF CHILDREN

Children must be supervised in use of this product.

INDICATIONS AND USAGE

- wet hands thoroughly with product
- briskly rub hands together until dry
- supervise children under 6 years in the use of this product

WARNINGS

For external use only.
Flammable. Keep away from fire or flame.

Do not use in ears and mouth. In case of contact, flush eyes thoroughly with water.

Stop using and ask a doctor, if irritation and redness develop and persist for more than 72 hours.

OTHER INFORMATION: store at 20-25 Celsius Degree (68 - 77 Fahrenheit), may discolor fabrics.

DOSAGE AND ADMINISTRATION

wet hands thoroughly with product, briskly rub with hands together until dry, supervise children under 6 years in the use of this product.

INACTIVE INGREDIENT

Water (Aqua), Glycerin, Carbomer, Triethanolamine, Propylene Glycol, Tocopheryl Acetate, Aloe Barbadensis Leaf Juice